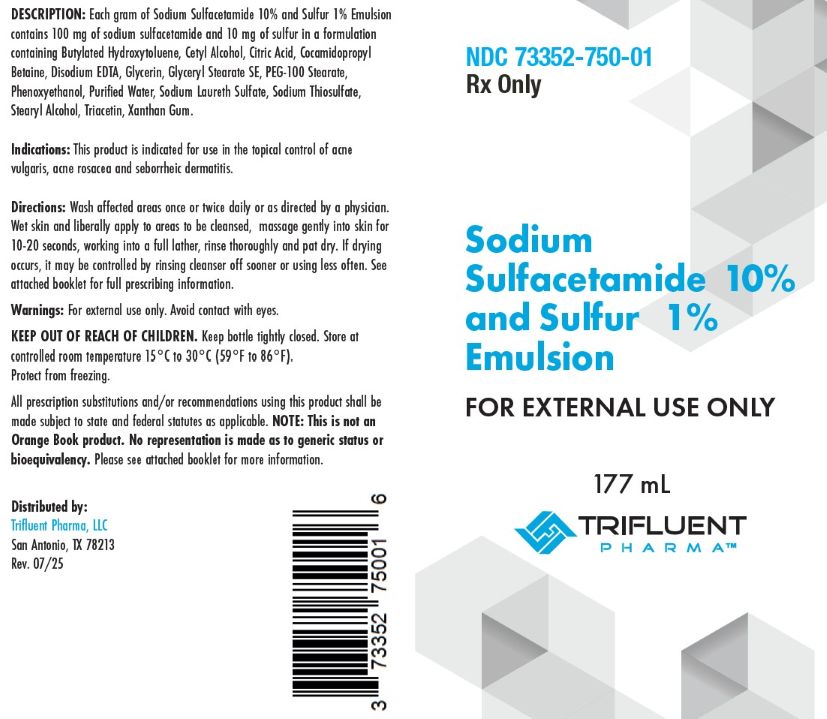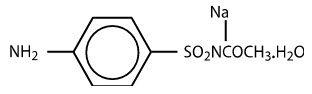 DRUG LABEL: Sodium Sulfacetamide and Sulfer Emulsion
NDC: 73352-750 | Form: EMULSION
Manufacturer: Trifluent Pharma
Category: prescription | Type: HUMAN PRESCRIPTION DRUG LABEL
Date: 20251015

ACTIVE INGREDIENTS: SULFACETAMIDE SODIUM 100 mg/1 mL; SULFUR 10 mg/1 mL
INACTIVE INGREDIENTS: GLYCERIN; MAGNESIUM DISODIUM EDTA; XANTHAN GUM; BUTYLATED HYDROXYTOLUENE; CETYL ALCOHOL; COCAMIDOPROPYL BETAINE; PEG-100 STEARATE; WATER; SODIUM THIOSULFATE; STEARYL ALCOHOL; TRIACETIN; SODIUM LAURETH SULFATE; PHENOXYETHANOL; GLYCERYL STEARATE SE; CITRIC ACID

Sodium Sulfacetamide 10% - Sulfur 1% Emulsion

NDC 773352-750-01

Sodium Sulfacetamide 10 % and Sulfur 1% Emulsion

Rx Only

FOR EXTERNAL USE ONLY. NOT FOR OPHTHALMIC USE.

Net. Wt. 177 mL

Active ingredients: Sodium Sulfacetamide 10% and Sulfer 1%

Indications: For the topical control of acne vulgaris, acne rosacea and seborrheic dermatitis.

Directions: Wash affected areas once or twice daily or as directed by a physician. Wet skin and liberally apply to areas to be cleansed, message gently into skin for 10-20 seconds, working into a full lather, rinse thoroughly and pat dry. If drying occurs, it may be controlld by rinsing cleanser off sooner or using less often. See attached booklet for full prescribing information.

Warning: for external use only.

Avoid Contract with eyes.

KEEP OUT OF REACH OF CHILDREN.

Keep bottle tightly closed.

Store at controlled room temperatures, 15º - 30ºC (59º - 86º F).

Protect from freezing.

All prescription substitutions and or recommendations using this product shall be made subject to the state and federal statutes as applicable. NOTE: This is not an Orange Book product. No representation is made as to generic status or bioequivalency. Please see attached booklet fo more information.

Distributed by:

Trifluent Pharma, LLC

San Antonio, TX 78212

Rev. 07-255

Rx Only

DESCRIPTION

Each gram of Sodium Sulfacetamide 10% and Sulfur 1% Emulsion contains 100 mg of sodium sulfacetamide and 10 mg of sulfur in a formulation containing Butylated Hydroxytoluene, Cetyl Alcohol, Citric Acid, Cocamidopropyl
Betaine, Disodium EDTA, Glycerin, Glyceryl Stearate SE, PEG-100 Stearate, Phenoxyethanol, Purified Water, Sodium Laureth Sulfate, Sodium Thiosulfate, Stearyl Alcohol, Triacetin, Xanthan Gum.

Sodium sulfacetamide is a sulfonamide with antibacterial activity while sulfur acts as a keratolytic agent. Chemically sodium sulfacetamide is N-[(4-aminophenyl) sulfonyl]-acetamide, monosodium salt, monohydrate. The structural formula is:

CLINICAL PHARMACOLOGY

The most widely accepted mechanism of action of sulfonamides is the Woods-Fildes theory, which is based on the fact that
sulfonamides act as competitive antagonists to para-aminobenzoic acid (PABA), an essential component for bacterial growth. While absorption through intact skin has not been determined, sodium sulfacetamide is readily absorbed from the
gastrointestinal tract when taken orally and excreted in the urine, largely unchanged. The biological half-life has variously been reported as 7 to 12.8 hours. The exact mode of action of sulfur in the treatment of acne is known, but it has been
reported that it inhibits the growth of Propionibacterium acnes and the formation of free fatty acids.

INDICATIONS

Sodium Sulfacetamide 10% - Sulfur 1% Emulsion is indicated in the topical control of acne vulgaris, acne rosacea and seborrheic dermatitis.

CONTRAINDICATIONS

Sodium Sulfacetamide 10% and Sulfur 1% Emulsion is contraindicated for use by patients having known hypersensitivity to sulfonamides, sulfur or any other component of this preparation.

Sodium Sulfacetamide 10% and Sulfer 1% Emulsion is not to be used by patietns with kidney disease.

WARNINGS

Although rare, sensitivity to sodium sulfacetamide may occur.
Therefore, caution and careful supervision should be observed when prescribing this
drug for patients who may be prone to hypersensitivity to topical sulfonamides.
Systemic toxic reactions such as agranulocytosis, acute hemolytic anemia, purpura
hemorrhagica, drug fever, jaundice, and contact dermatitis indicate hypersensitivity
to sulfonamides. Particular caution should be employed if areas of denuded or abraded skin are involved.

FOR EXTERNAL USE ONLY. Keep away from eyes. Keep out of reach of children.
In case of accidental ingestion contact a poison control center immediately. Keep
container tightly closed.

PRECAUTIONS

-

General

If irritation develops, use of the product should be discontinued and appropriate therapy instituted. Patients should be carefully
observed for possible local irritation or sensitization during longterm therapy. The object of this therapy is to achieve desquamation without irritation, but sodium sulfacetamide and sulfur can cause reddening and scaling of the epidermis. These
side effects are not unusual in the treatment of acne vulgaris, but patients should be cautioned about the possibility.

Information for patients

Avoid contact with eyes, eyelids, lips and mucous membranes. If accidental contact occurs, rinse with water. If excessive irritation
develops, discontinue use and consult your physician.

Carcinogenesis, Mutagenesis and Impairment of Fertility

Long-term studies in animals have not been performed to evaluate carcinogenic potential.

PREGNANCY

-

Category C

Animal reproduction studies have not been conducted with Sodium Sulfacetamide 10% and Sulfer 1% Emulsion. It is not known whether Sodium Sulfacetamide 10% and Sulfer 1% Emulsion can cause fetal harm when administered to a pregnant woman or can affect reproduction capacity. Sodium Silfacetamide 10% and Sulfer 1% Emulsion should be given to a pregnant woman only if clearly needed.

NURSING MOTHERS

It is not known whether sodium sulfacetamide is excreted in the human milk following topical use of Sodium Sulfacetamide 10% and Sulfur 1% Emulsion. However, small amounts of orally administered sulfonamides have been reported to be eliminated in human milk. In view of this and because many drugs are excreted in human milk, caution should be exercised when Sodium Sulfacetamide 10%
and Sulfur 1% Emulsion is administered to a nursing woman.

PEDIATRIC USE

Safety and effectiveness in children under the age of 12 have not been established.

ADVERSE REACTIONS

Although rare, sodium sulfacetamide may cause local irritation.

Call your doctor for medical advice about side effects. To report a serious
adverse event, please contact Trifluent Pharma, LLC at 1-888-927-5191.

DOSAGE AND ADMINISTRATION

Apply Sodium Sulfacetamide 10% and Sulfur 1% Emulsion once or twice daily to affected areas, or as directed by your physician.
Wet skin and liberally apply to areas to be cleansed. Massage gently into skin for 10-20 seconds, working into a full lather, rinse
thoroughly and pat dry. If drying occurs, it may be controlled by rinsing off Sodium Sulfacetamide 10% and Sulfur 1% Emulsion sooner or using less often.

HOW SUPPLIED

Sodium Sulfacetamide 10% and Sulfur 1% Emulsion is available
in 177 mL bottles, NDC 73352-750-01.

STORAGE AND HANDLING

Store at controlled room temperature, 15° - 30°C (59° - 86°F). Protect from freezing.

KEEP THIS AND ALL MEDICATIONS OUT OF THE REACH OF CHILDREN.

Distributed by

Trifluent Pharma, LLC.

San Antonio, Tx 78213

All prescription substitutions and or recommendations using this product shall be made subject to state and federal statutes as applicable. Note: This is not an Orange Book product. No representation is made as to the generic satus or bioequivalency. Each person recommending a prescription substitution using this product shall make such recommendationss based on each such person's professonal opinion and knowlege, upon evaluating the active ingredients, excipients, inactive ingredients and chemical formulation provided herein.

PRINCIPAL DISPLAY PANEL - 177 mL Bottle Label

NDC 73352-750-01

Rx Only

Sodium Sulfacetamide 10% Sulfur 1% Emulsion

FOR EXTERNAL USE ONLY
NOT FOR OPHTHALMIC USE

Net Wt. 177mL

Trifluent Pharma, LLC

San Antonio TX 78213